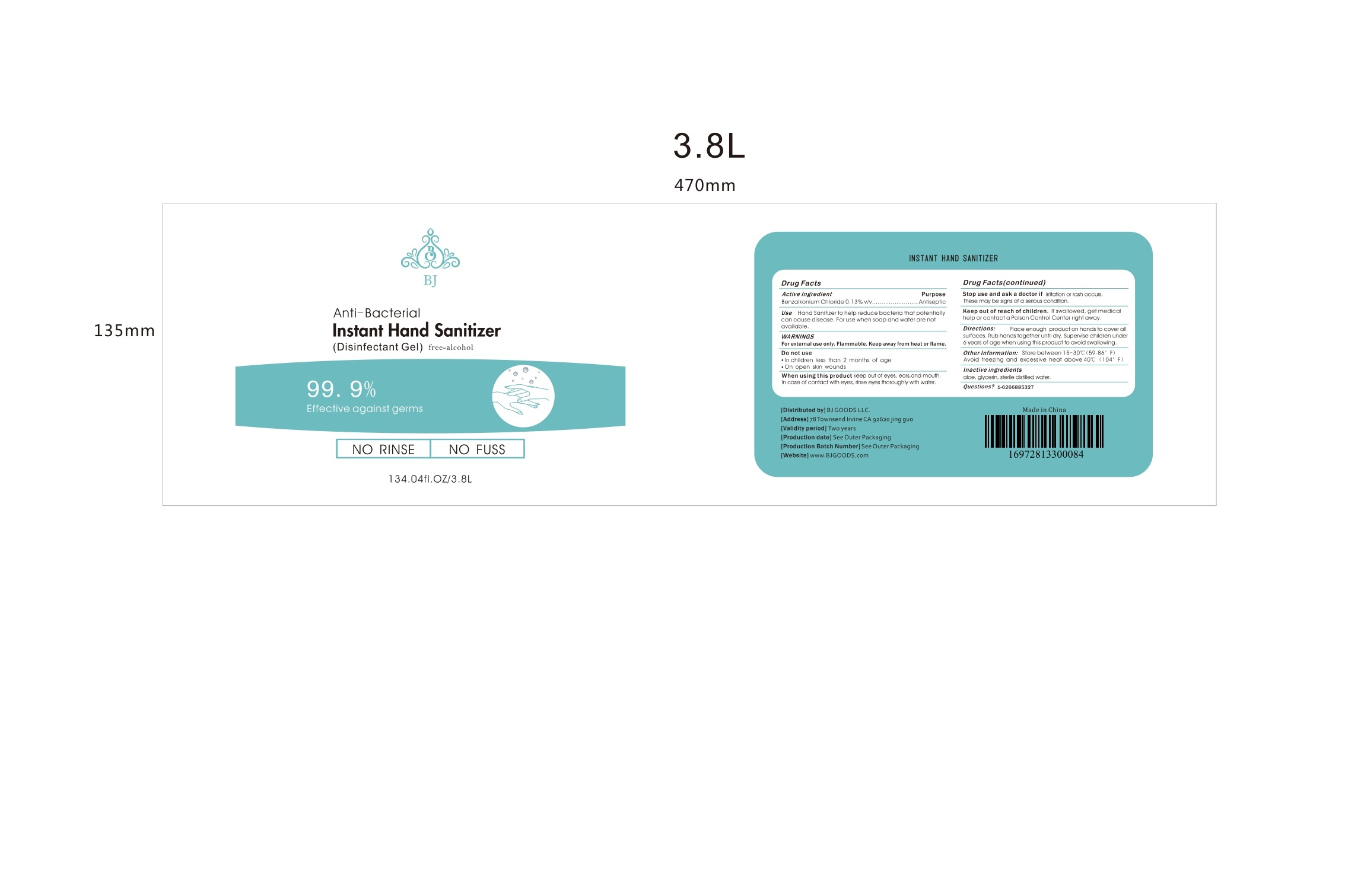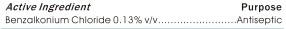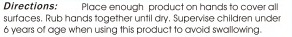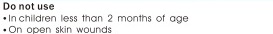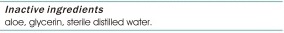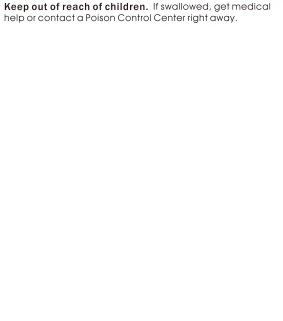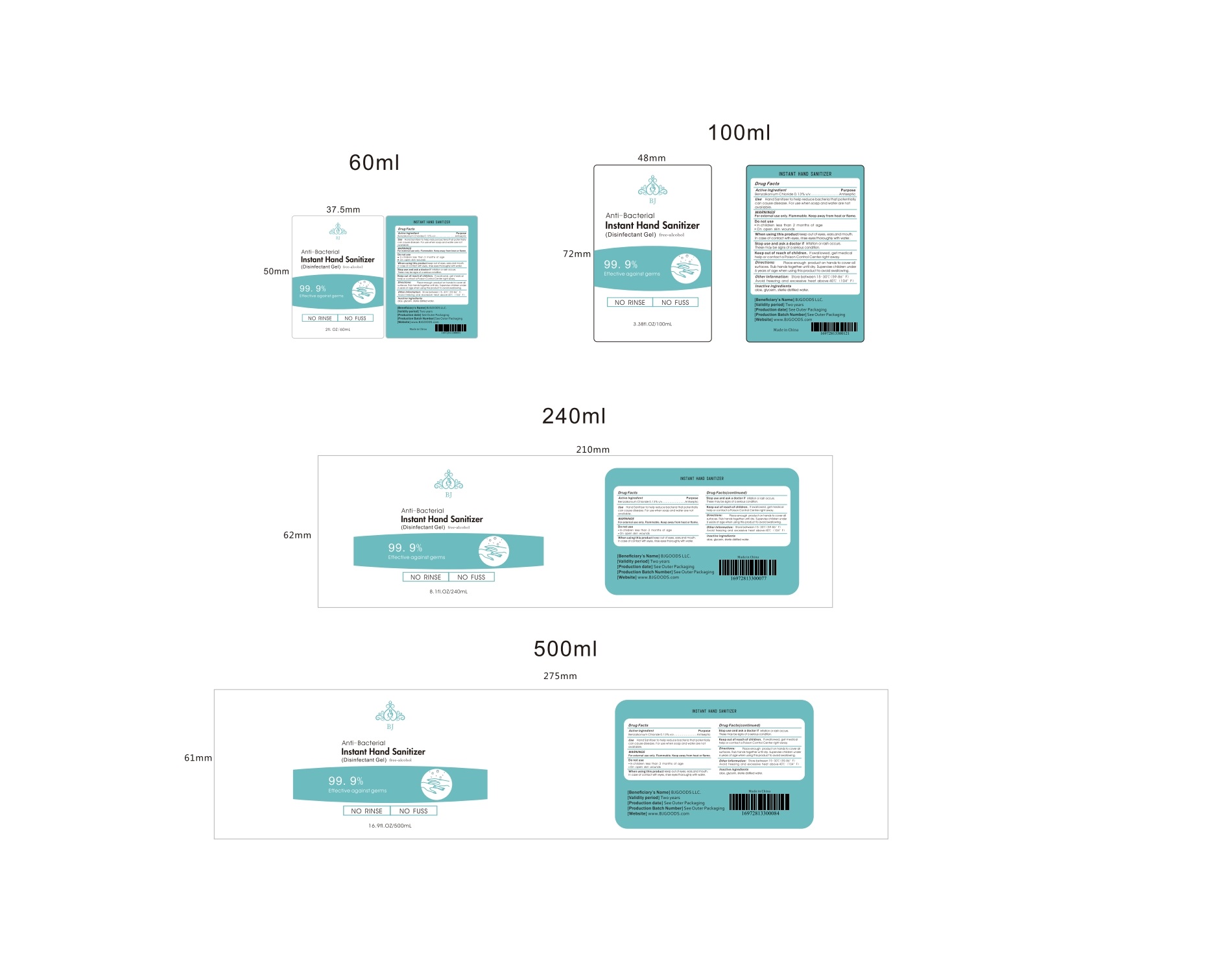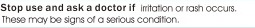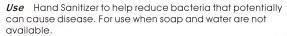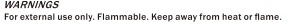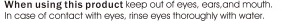 DRUG LABEL: 0.13% Benzalkonium Chloride Instant Hand sanitizer
NDC: 79635-019 | Form: GEL
Manufacturer: BJ Goods LLC
Category: otc | Type: HUMAN OTC DRUG LABEL
Date: 20200707

ACTIVE INGREDIENTS: BENZALKONIUM CHLORIDE 0.14 g/100 mL
INACTIVE INGREDIENTS: BENZETHONIUM CHLORIDE 0.1 g/100 mL; CHLORHEXIDINE GLUCONATE 0.1 g/100 mL; ALOE VERA LEAF 0.09 g/100 mL; HYDROXYETHYL CELLULOSE (2000 MPA.S AT 1%) 0.5 g/100 mL; WATER 96.08 g/100 mL; GLYCERIN 3 g/100 mL

Keep out of reach of children

INDICATIONS AND USAGE

Directions: Place enough product on hands to cover all surfaces. Rub hands together until dry. Supervise children under 6 years of age when using this product to avoid swallowing.

PURPOSE

Use: Hand sanitizer to help reduce bacteria that potentially can cause disease. For use when soap and water are not available.

Dosage form: Gel

Directions: Place enough product on hands to cover all surfaces. Rub hands together until dry. Supervise children under 6 years of age when using this product to avoid swallowing.

ACTIVE INGREDIENT

Benzalkonium Chloride 0.13% v/v

WARNINGS

Warnings: For external use only. Flammable. Keep away from heat or flame.

Do not use: In children less than 2 months of age. On open skin wounds.

When using this product: Keep out of eyes, ears, and mouth. In case of contact with eyes, rinse eyes thoroughly with water.

Stop use and ask a doctor if: irritation or rash occurs. These may by signs o a serious condition.

INACTIVE INGREDIENT

Aloe, glycerin, sterile distilled water

PACKAGE LABEL

Anti-Bacterial Hand Sanitizer (Disinfectant Gel) free - alcohol

3.8L label NDC: 79635-019-05

60 ml label NDC:79635-019-01

100 ml label NDC: 79635-019-02

240 ml label NDC: 79635-019-03

500 ml label NDC: 79635-019-04